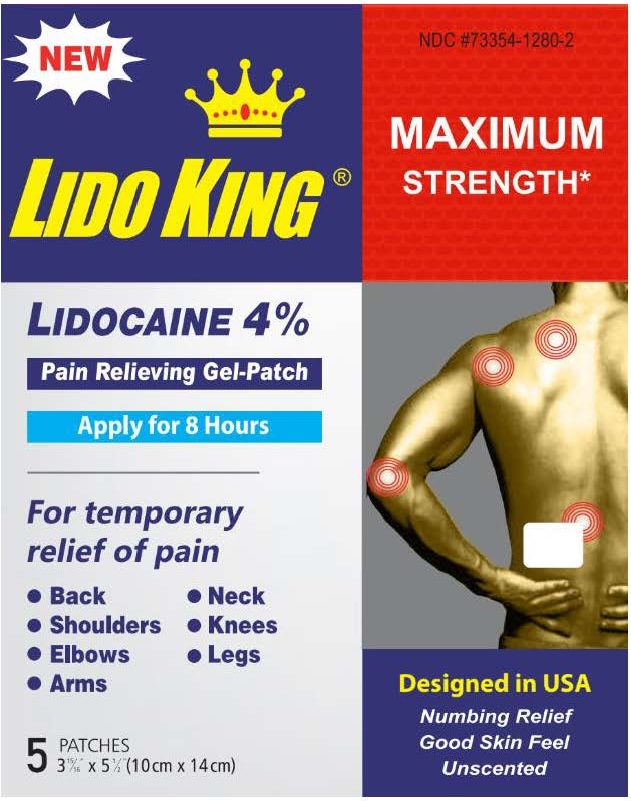 DRUG LABEL: Lido King Lidocaine 4% Pain Relieving Gel-Patch
NDC: 73354-1280 | Form: PATCH
Manufacturer: Galaxy Bio, Inc.
Category: otc | Type: HUMAN OTC DRUG LABEL
Date: 20241001

ACTIVE INGREDIENTS: LIDOCAINE 4 g/100 g
INACTIVE INGREDIENTS: POLYSORBATE 80; POVIDONE K90; DIHYDROXYALUMINUM AMINOACETATE; EDETATE DISODIUM; GLYCERIN; KAOLIN; METHYLPARABEN; POLYACRYLIC ACID (450000 MW); PROPYLENE GLYCOL; PROPYLPARABEN; WATER; SODIUM POLYACRYLATE (2500000 MW); TARTARIC ACID; TITANIUM DIOXIDE

LIDO KING- lidocaine patch

Active ingredient

Lidocaine 4%

Purpose

Topical anesthetic

Uses

For temporary relief of pain

Warnings

For external use only

Do not use

- if you are allergic to any ingredients of this product
- more than one patch at a time
- on wounds or damaged skin
- with a heating pad
- if pouch is damaged or opened

When using this product

- avoid contact with the eyes, mucous membranes or rashes
- use only as directed
- do not bandage tightly
- do not reuse patch

Stop use and ask a doctor if

- localized skin reactions occur, such as rash, itching, redness, irritation, pain, swelling and blistering
- symptoms clear up and occur again within a few days
- symptoms persist for more than 7 days
- conditions worsen

If pregnant or breast-feeding,

ask a health professional before use.

Keep out of reach of children.

If swallowed, get medical help or contact a Poison Control Center right away.

Directions

Adults and children 12 years of age and over:

- clean and dry affected area
- remove film from patch and apply to the skin (see illustration)
- apply to affected area not more than 3 to 4 times daily
- remove patch from the skin after at most 8-hour application

Children under 12 years of age: consult a doctor

Other information

- store in a cool dry place
- protect product from freezing, excessive heat and moisture
- avoid storing product in direct sunlight

Inactive ingredients

dihydroxyaluminum aminoacetate, edetate disodium, glycerin, kaolin, methylparaben, polyacrylic acid, propylene glycol, propylparaben, polysorbate 80, polyvinylpyrrolidone k90, purified water, sodium polyacrylate, tartaric acid, titanium dioxide

Questions or comments?

Toll free 1-888-894-8002 www.lidokingpatch.com

Principal Display Panel

LIDO KING ®

NDC# 73354-1280-2

MAXIMUM

STRENGTH*

LIDOCAINE 4%

Pain Relieving Gel-Patch

Apply for 8 Hours

Designed in USA

Numbing Relief

Good Skin Feel

Unscented

For temporary relief of pain

• Back

• Neck

• Shoulders

• Knees

• Elbows

• Legs

• Arms

5 PATCHES

3 15/16" x 5 1/2" (10 cm x 14 cm)

For Galaxy Bio, Inc.

Cranbury, NJ 08512

Made in China

* Available without a prescription

®Registered Trademark of NAL Pharma